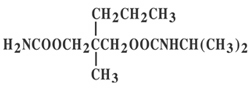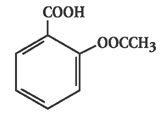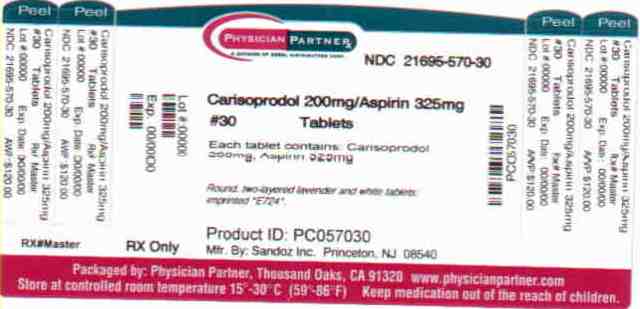 DRUG LABEL: Carisoprodol and Aspirin
NDC: 21695-570 | Form: TABLET
Manufacturer: Rebel Distributors Corp
Category: prescription | Type: HUMAN PRESCRIPTION DRUG LABEL
Date: 20101210

ACTIVE INGREDIENTS: CARISOPRODOL 200 mg/1 1; ASPIRIN 325 mg/1 1
INACTIVE INGREDIENTS: SILICON DIOXIDE; STARCH, CORN; CROSCARMELLOSE SODIUM; FD&C BLUE NO. 1; D&C RED NO. 30; MAGNESIUM STEARATE; CELLULOSE, MICROCRYSTALLINE; POVIDONE; STEARIC ACID

CARISOPRODOL AND ASPIRIN 200MG/325MG USP Rx Only

DESCRIPTION

Carisoprodol and Aspirin Tablets, USP is a combination product containing carisoprodol, a centrally-acting muscle relaxant, plus aspirin, an analgesic with antipyretic and antiinflammatory properties.

Chemically, carisoprodol is (+)-2-Methyl-2-propyl-1,3-propanediol carbamate isopropylcarbamate. Carisoprodol is a white, crystalline powder, having a mild, characteristic odor and a bitter taste. It is very slightly soluble in water; freely soluble in alcohol, in chloroform, and in acetone. Its molecular formula is C12H24N204, with a molecular weight of 260.34. The structural formula is:

Chemically, aspirin is salicylic acid acetate. It can appear as white crystals, commonly tabular or needle-like, or white crystalline powder. It is odorless or has a faint odor. It is slightly soluble in water; freely soluble in alcohol; soluble in chloroform and in ether; sparingly soluble in absolute ether. Its molecular formula is C

9

H

8

0

4

, with a molecular weight of 180.16. The structural formula is:

Each tablet, for oral administration, contains 200 mg of carisoprodol and 325 mg of aspirin. In addition, each tablet contains the following inactive ingredients: Colloidal silicon dioxide, corn starch, croscarmellose sodium, FD and C Blue #1, D and C #30 Aluminum Lake, magnesium stearate, microcrystalline cellulose, povidone, and stearic acid.

CLINICAL PHARMACOLOGY

Carisoprodol: Carisoprodol is a centrally-acting muscle relaxant that does not directly relax tense skeletal muscles in man. The mode of action of carisoprodol in relieving acute muscle spasm of local origin has not been clearly identified, but may be related to its sedative properties. In animals, carisoprodol has been shown to produce muscle relaxation by blocking interneuronal activity and depressing transmission of polysynaptic neurons in the spinal cord and in the descending reticular formation of the brain. The onset of action is rapid and lasts four to six hours.

Carisoprodol is metabolized in the liver and is excreted by the kidneys. It is dialyzable by peritoneal and hemodialysis.

Aspirin: Aspirin is a nonnarcotic analgesic with antiinflammatory and antipyretic activity. Inhibition of prostaglandin biosynthesis appears to account for most of its antiinflammatory and for at least part of its analgesic and antipyretic properties.

Aspirin is rapidly absorbed and almost totally hydrolyzed to salicylic acid following oral administration. Although aspirin has a half-life of only about 15 minutes, the apparent biologic half-life of salicylic acid in the therapeutic plasma concentration range is between 6 and 12 hours. Salicylic acid is eliminated by renal excretion and by biotransformation to inactive metabolites. Clearance of salicylic acid in the high-dose range is sensitive to urinary pH (see Drug Interactions) and is reduced by renal dysfunction.

INDICATIONS AND USAGE

Carisoprodol and Aspirin Tablets are indicated as an adjunct to rest, physical therapy, and other measures for the relief of pain, muscle spasm, and limited mobility associated with acute, painful musculoskeletal conditions.

CONTRAINDICATIONS

Acute intermittent porphyria; bleeding disorders; allergic or idiosyncratic reactions to carisoprodol, aspirin, or related compounds.

WARNINGS

On very rare occasions, the first dose of carisoprodol has been followed by an idiosyncratic reaction with symptoms appearing within minutes or hours. These may include extreme weakness, transient quadriplegia, dizziness, ataxia, temporary loss of vision, diplopia, mydriasis, dysarthria, agitation, euphoria, confusion, and disorientation. Although symptoms usually subside over the course of the next several hours, discontinue Carisoprodol and Aspirin Tablets and initiate appropriate supportive and symptomatic therapy, which may include epinephrine and/or antihistamines. In severe cases, corticosteroids may be necessary. Severe reactions have been manifested by asthmatic episodes, fever, weakness, dizziness, angioneurotic edema, smarting eyes, hypotension, and anaphylactoid shock.

The effects of carisoprodol with agents such as alcohol, other CNS depressants, or psychotropic drugs may be additive. Appropriate caution should be exercised with patients who may take one or more of these agents simultaneously with Carisoprodol and Aspirin Tablets.

PRECAUTIONS

General

To avoid excessive accumulation of carisoprodol, aspirin, or their metabolites, use Carisoprodol and Aspirin Tablets with caution in patients with compromised liver or kidney function, or in elderly or debilitated patients (see CLINICAL PHARMACOLOGY).

Use with caution in patients with history of gastritis or peptic ulcer, in patients on anticoagulant therapy, and in addiction-prone individuals.

Information for Patients

Caution patients that this drug may impair the mental and/or physical abilities required for the performance of potentially hazardous tasks such as driving a motor vehicle or operating machinery.

Caution patients with a predisposition for gastrointestinal bleeding that concomitant use of aspirin and alcohol may have an additive effect in this regard.

Caution patients that dosage of medications used for gout, arthritis, or diabetes may have to be adjusted when aspirin is administered or discontinued (see Drug Interactions).

Drug Interactions

Clinically important interactions may occur when certain drugs are administered concomitantly with aspirin or aspirin-containing drugs.

1. Oral Anticoagulants-By interfering with platelet function or decreasing plasma prothrombin concentration, aspirin enhances the potential for bleeding in patients on anticoagulants.

2. Methotrexate-aspirin enhances the toxic effects of this drug.

3. Probenecid and Sulfinpyrazone-large doses of aspirin reduce the uricosuric effect of both drugs. Renal excretion of salicylate may also be reduced.

4. Oral Antidiabetic Drugs-enhancement of hypoglycemia may occur.

5. Antacids-to the extent that they raise urinary pH, antacids may substantially decrease plasma salicylate concentrations; conversely, their withdrawal can result in a substantial increase.

6. Ammonium Chloride-this and other drugs that acidify a relatively alkaline urine can elevate plasma salicylate concentrations.

7. Ethyl Alcohol-enhanced aspirin-induced fecal blood loss has been reported.

8. Corticosteroids-salicylate plasma levels may be decreased when adrenal corticosteroids are given, and may be increased substantially when they are discontinued.

Carcinogenesis, Mutagenesis, Impairment of Fertility

No long-term studies have been done with Carisoprodol and Aspirin Tablets.

Pregnancy

Teratogenic Effects

Pregnancy Category C .Adequate animal reproduction studies have not been conducted with Carisoprodol and Aspirin Tablets. It is also not known whether Carisoprodol and Aspirin Tablets can cause fetal harm when administered to a pregnant woman or can affect reproduction capacity. Carisoprodol and Aspirin Tablets should be given to a pregnant woman only if clearly needed. Studies in rodents have shown salicylates to be teratogenic when given in early gestation, and embryocidal when given in later gestation in doses considerably greater than usual therapeutic doses in humans. Studies in women who took aspirin during pregnancy have not demonstrated an increased incidence of congenital abnormalities in the offspring.

Labor and Delivery

Ingestion of aspirin near term or prior to delivery may prolong delivery or lead to bleeding in mother, fetus, or neonate.

Nursing Mothers

Carisoprodol is excreted in human milk in concentrations two-to-four times that in maternal plasma. Aspirin is excreted in human milk in moderate amounts and can produce a bleeding tendency in nursing infants. Because of the potential for serious adverse reactions in nursing infants a decision should be made whether to discontinue nursing or the drug, taking into account the importance of the drug to the mother.

Pediatric Use

Safety and effectiveness in pediatric patients below the age of twelve have not been established.

ADVERSE REACTIONS

If severe reactions occur, discontinue Carisoprodol and Aspirin Tablets and initiate appropriate symptomatic and supportive therapy.

The following side effects which have occurred with the administration of the individual ingredients alone may also occur with the combination.

Carisoprodol:

Central Nervous System: Drowsiness is the most frequent complaint and along with other CNS effects may require dosage reduction. Observed less frequently are dizziness, vertigo and ataxia. Tremor, agitation, irritability, headache, depressive reactions, syncope and insomnia have been infrequent or rare.

Idiosyncratic: Idiosyncratic reactions are very rare. They are usually seen within the period of the first to fourth dose in patients having had no previous contact with the drug (see WARNINGS).

Allergic: Skin rash erythema multiforme, pruritus, eosinophilia and fixed drug eruptions with cross-reaction to meprobamate have been reported. If allergic reactions occur, discontinue Carisoprodol and Aspirin Tablets and treat symptomatically. In evaluating possible allergic reactions, also consider allergy to excipients.

Cardiovascular: Tachycardia, postural hypotension and facial flushing.

Gastrointestinal: Nausea, vomiting, epigastric distress and hiccup.

Hematologic: No serious blood dyscrasias have been attributed to carisoprodol alone.

Leukopenia and pancytopenia have been reported, very rarely, in situations in which other drugs or viral infections may have been responsible.

Aspirin:

The most common adverse reactions associated with the use of aspirin have been gastrointestinal, including nausea, vomiting, gastritis, occult bleeding, constipation and diarrhea. Gastric erosion, angioedema, asthma rash, pruritus and urticaria have been reported less commonly. Tinnitus is a sign of high serum salicylate levels (see OVERDOSAGE).

Aspirin Intolerance: Allergic type reactions in aspirin-sensitive individuals may involve the respiratory tract or the skin. Symptoms of the former range from rhinorrhea and shortness of breath to severe asthma, and the latter may consist of urticaria, edema, rash or angioedema (giant hives). These may occur independently or in combination.

DRUG ABUSE AND DEPENDENCE

Abuse: In clinical use, abuse has been rare.

Dependence: In clinical use, dependence with Carisoprodol and Aspirin Tablets have been rare and there have been no reports of significant abstinence signs, nevertheless, the following information on the individual ingredients should be kept in mind.

Carisoprodol: In dogs, no withdrawal symptoms occurred after abrupt cessation of carisoprodol from dosages as high as 1 gm/kg/day. In a study in man, abrupt cessation of 100 mg/kg/day (about five times the recommended daily adult dosage) was followed in some subjects by mild withdrawal symptoms such as abdominal cramps, insomnia, chills, headache and nausea. Delirium and convulsions did not occur (see PRECAUTIONS).

OVERDOSAGE

Signs and Symptoms: Any of the following which have been reported with the individual ingredients may occur and may be modified to a varying degree by the effects of the other ingredients present in Carisoprodol and Aspirin Tablets.

Carisoprodol: Stupor, coma, shock, respiratory depression and very rarely, death. Overdosage with carisoprodol in combination with alcohol, other CNS depressants, or psychotropic agents can have additive effects, even when one of the agents has been taken in the usually recommended dosage.

Aspirin: Headache, tinnitus, hearing difficulty, dim vision, dizziness, lassitude, hyperpnea, rapid breathing, thirst, nausea, vomiting, sweating and occasionally diarrhea are characteristic of mild to moderate salicylate poisoning. Salicylate poisoning should be considered in children with symptoms of vomiting, hyperpnea, and hyperthermia.

Hyperpnea is an early sign of salicylate poisoning, but dyspnea supervenes at plasma levels above 50 mg/dl. These respiratory changes eventually lead to serious acid-base disturbances, Metabolic acidosis is a constant finding in infants but occurs in older children only with severe poisoning; adults usually exhibit respiratory alkalosis initially and acidosis terminally.

Other symptoms of severe salicylate poisoning include hyperthermia, dehydration, delirium and mental disturbances. Skin eruptions, GI hemorrhage, or pulmonary edema are less common.

Early CNS stimulation is replaced by increasing depression, stupor, and coma. Death is usually due to respiratory failure or cardiovascular collapse.

Treatment:

General: Provide symptomatic and supportive treatment, as indicated. Any drug remaining in the stomach should be removed using appropriate procedures and caution to protect the airway and prevent aspiration, especially in the stuporous or comatose patient. Incomplete gastric emptying with delayed absorption of carisoprodol has been reported as a cause for relapse. Should respiration or blood pressure become compromised, respiratory assistance, central nervous system stimulants and pressor agents should be administered cautiously as indicated.

Carisoprodol: The following have been used successfully in overdosage with the related drug meprobamate: diuretics, osmotic (mannitol) diuresis, peritoneal dialysis, and hemodialysis (see CLINICAL PHARMACOLOGY). Careful monitoring of urinary output is necessary and caution should be taken to avoid overhydration. Carisoprodol can be be measured in biological fluid by gas chromatography (Douglas, J.F., et al: J Pharm Sci 58:145, 1969).

Aspirin: Since there are no specific antidotes for salicylate poisoning, the aim of treatment is to enhance elimination of salicylate and prevent or reduce further absorption; to correct any fluid electrolyte or metabolic imbalance; and to provide general and cardiorespiratory support. If acidosis is present, intravenous sodium bicarbonate must be given, along with adequate hydration, until salicylate levels decrease to within the therapeutic range. To enhance elimination, forced diuresis and alkalinization of the urine may be beneficial. The need for hemoperfusion or hemodialysis is rare and should be used only when other measures have failed.

DOSAGE AND ADMINISTRATION

Usual Adult Dosage: 1 or 2 tablets, four times daily.

Not recommended for use in children under age twelve (see PRECAUTIONS).

HOW SUPPLIED

Tablets containing Carisoprodol 200 mg and Aspirin 325 mg are white and light lavender colored with double layered round shape, unscored debossed with E724 and are available as follows

- 21695-570-30 Bottle of 30
- 21695-570-60 Bottle of 60

Store at controlled room temperature 15°C - 30°C (59°F - 86°F) protect from moisture.

Dispense in a tight, light-resistant container as defined in the USP, with a child-resistant closure (as required).

Manufactured by Epic Pharma, LLC

Laurelton, NY 11413

Manufactured for Sandoz Inc.

Princeton, NJ 08540

Repackaged by:
Rebel Distributors Corp
Thousand Oaks, CA 91320

PACKAGE LABEL, PRINCIPLE DISPLAY PANEL

30 Tablets NDC 21695-570-30
Carisoprodol and Aspirin Tablets, USP
Rx Only 200mg/325mg
Each Tablet Contains:
Carisoprodol 200mg
Aspirin 325mg